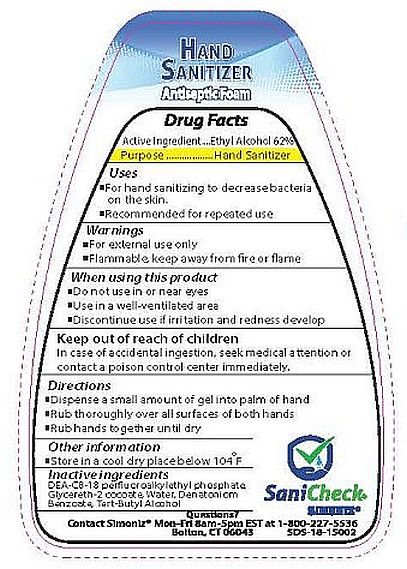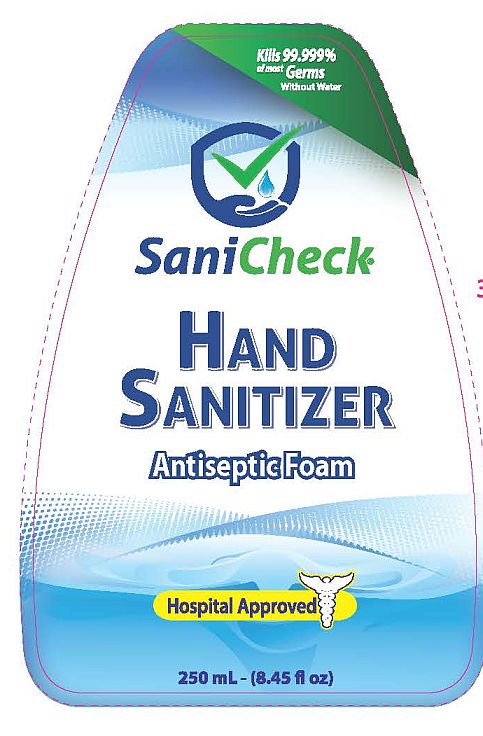 DRUG LABEL: Hand Sanitizer
NDC: 63900-130 | Form: LIQUID
Manufacturer: Simoniz USA, Inc.
Category: otc | Type: HUMAN OTC DRUG LABEL
Date: 20181231

ACTIVE INGREDIENTS: ALCOHOL 62 mL/100 mL
INACTIVE INGREDIENTS: WATER; GLYCERETH-2 COCOATE; DENATONIUM BENZOATE; TERT-BUTYL ALCOHOL; DIETHANOLAMINE BIS(C8-C18 PERFLUOROALKYLETHYL)PHOSPHATE

SaniCheck Hand Sanitizer

Active ingredient

Ethyl Alcohol 62%

Purpose

Hand Sanitizer

Uses

- For hand sanitizing to decrease bacteria on the skin.
- Recommended for repeated use

Warnings

- For external use only
- Flammable, keep away from fire or flame

When using this product

- Do not use in or near eyes
- Use in a well-ventilated area
- Discontinue use if irritation and redness develop

Keep out of reach of children

In case of accidental ingestion, seek medical attention or contact a poison control center immediately.

Directions

- Dispense a small amount of gel into palm of hand
- Rub thoroughly over all surfaces of both hands
- Rub hands together until dry

Other information

- Store in a cool dry place below 104°F

Inactive ingredients

DEA-C8-18 perfluoroalkylethyl phosphate, Glycereth-2 cocoate, Water, Denatoniom Benzoate, Tert-Butyl Alcohol

Questions?

Contact Simoniz Mon-Fri 8am-5pm EST at 1-800-227-5536

Bolton, CT 06043

SaniCheck

HAND SANITIZER

Antiseptic Foam

Kills 99.999% of most Germs Without Water

Hospital Approved

250 mL - (8.45 fl oz)